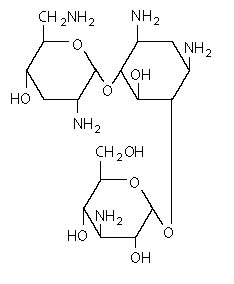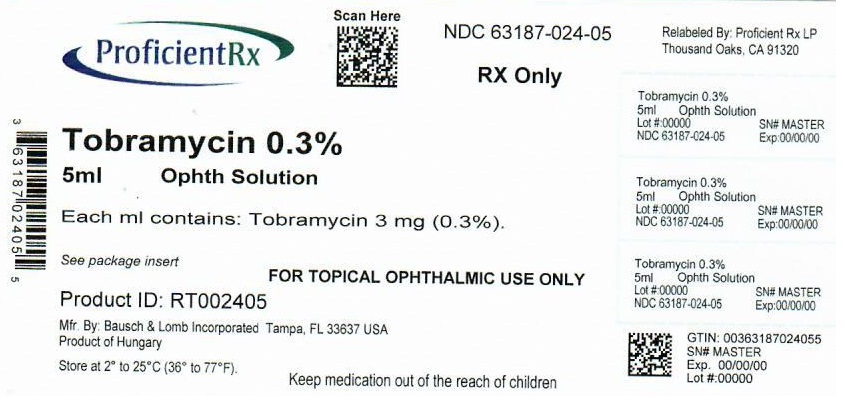 DRUG LABEL: Tobramycin
NDC: 63187-024 | Form: SOLUTION
Manufacturer: Proficient Rx LP
Category: prescription | Type: HUMAN PRESCRIPTION DRUG LABEL
Date: 20220701

ACTIVE INGREDIENTS: TOBRAMYCIN 3 mg/1 mL
INACTIVE INGREDIENTS: BENZALKONIUM CHLORIDE 0.1 mg/1 mL; BORIC ACID; WATER; SODIUM CHLORIDE; SODIUM HYDROXIDE; SODIUM SULFATE; SULFURIC ACID; TYLOXAPOL

Tobramycin
Ophthalmic Solution USP,
0.3% (Sterile)

Rx only

DESCRIPTION:

Tobramycin ophthalmic solution is a sterile topical ophthalmic antibiotic formulation prepared specifically for topical therapy of external infections.

EACH mL CONTAINS:

ACTIVE: Tobramycin 3 mg (0.3%). INACTIVES: Boric Acid, Sodium Sulfate, Sodium Chloride, Tyloxapol and Purified Water. Sodium Hydroxide and/or Sulfuric Acid may be added to adjust pH (7.0 - 8.0).

PRESERVATIVE ADDED: Benzalkonium Chloride 0.1 mg (0.01%).

The structural formula of tobramycin is

Molecular formula: C18H37N5O9
Molecular weight: 467.52

Chemical name:

O-[3-amino-3-deoxy—α-D-gluco-pyranosyl-(1 → 4)]-O-[2,6-diamino-2,3,6-trideoxy-α-D-ribohexo-pyranosyl- (1 → 6)]-2-deoxystreptamine.

Tobramycin is a water-soluble aminoglycoside antibiotic active against a wide variety of gram-negative and gram-positive ophthalmic pathogens.

CLINICAL PHARMACOLOGY:

In Vitro Data: In vitro studies have demonstrated tobramycin is active against susceptible strains of the following microorganisms:

Staphylococci, including S. aureus and S. epidermidis (coagulase-positive and coagulase-negative), including penicillin-resistant strains.

Streptococci, including some of the Group A-betahemolytic species, some nonhemolytic species, and some Streptococcus pneumoniae.

Pseudomonas aeruginosa, Escherichia coli, Klebsiella pneumoniae, Enterobacter aerogenes, Proteus mirabilis, Morganella morganii, most Proteus vulgaris strains, Haemophilus influenzae and H. aegyptius, Moraxella lacunata, and Acinetobacter calcoaceticus and some Neisseria species. Bacterial susceptibility studies demonstrate that in some cases, microorganisms resistant to gentamicin retain susceptibility to tobramycin. A significant bacterial population resistant to tobramycin has not yet emerged; however, bacterial resistance may develop upon prolonged use.

INDICATIONS AND USAGE:

Tobramycin Ophthalmic Solution is a topical antibiotic indicated in the treatment of external infections of the eye and its adnexa caused by susceptible bacteria. Appropriate monitoring of bacterial response to topical antibiotic therapy should accompany the use of Tobramycin Ophthalmic Solution. Clinical studies have shown tobramycin to be safe and effective for use in children.

CONTRAINDICATIONS:

Tobramycin Ophthalmic Solution is contraindicated in patients with known hypersensitivity to any of its components.

WARNINGS:

NOT FOR INJECTION INTO THE EYE. Sensitivity to topically applied aminoglycosides may occur in some patients. If a sensitivity reaction to Tobramycin Ophthalmic Solution occurs, discontinue use.

PRECAUTIONS:

General:

As with other antibiotic preparations, prolonged use may result in overgrowth of nonsusceptible organisms, including fungi. If superinfection occurs, appropriate therapy should be initiated.

Information for patients:

Do not touch dropper tip to any surface, as this may contaminate the contents.

Pregnancy Category B.

Reproduction studies in three types of animals at doses up to thirty-three times the normal human systemic dose have revealed no evidence of impaired fertility or harm to the fetus due to tobramycin. There are, however, no adequate and well-controlled studies in pregnant women. Because animal studies are not always predictive of human response, this drug should be used during pregnancy only if clearly needed.

Nursing Mothers:

Because of the potential for adverse reactions in nursing infants from Tobramycin Ophthalmic Solution, a decision should be made whether to discontinue nursing the infant or discontinue the drug, taking into account the importance of the drug to the mother.

ADVERSE REACTIONS:

The most frequent adverse reactions to tobramycin ophthalmic solution is localized ocular toxicity and hypersensitivity, including lid itching and swelling, and conjunctival erythema. These reactions occur in less than three of 100 patients treated with tobramycin. Similar reactions may occur with the topical use of other aminoglycoside antibiotics. Other adverse reactions have not been reported from tobramycin therapy; however, if topical ocular tobramycin is administered concomitantly with systemic aminoglycoside antibiotics, care should be taken to monitor the total serum concentration.

OVERDOSAGE:

Clinically apparent signs and symptoms of an overdose of tobramycin ophthalmic solution (punctate keratitis, erythema, increased lacrimation, edema and lid itching) may be similar to adverse reaction effects seen in some patients.

DOSAGE AND ADMINISTRATION:

In mild to moderate disease, instill one or two drops into the affected eye(s) every four hours. In severe infections, instill two drops into the eye(s) hourly until improvement, following which treatment should be reduced prior to discontinuation.

DO NOT USE IF IMPRINTED NECKBAND IS NOT INTACT.

FOR OPHTHALMIC USE ONLY

HOW SUPPLIED:

Tobramycin Ophthalmic Solution USP, 0.3% is supplied in a plastic bottle with a controlled drop tip in the following size:

5 mL bottle – NDC 63187-024-05

Storage:

Store at 2°-25°C (36°-77°F). Avoid excessive heat.

KEEP OUT OF REACH OF CHILDREN.

Revised August 2007

Bausch & Lomb Incorporated
Tampa, FL 33637
©Bausch & Lomb Incorporated

9116801 (Folded)
9116901 (Flat)

Repackaged by:
Proficient Rx LP
Thousand Oaks, CA 91320